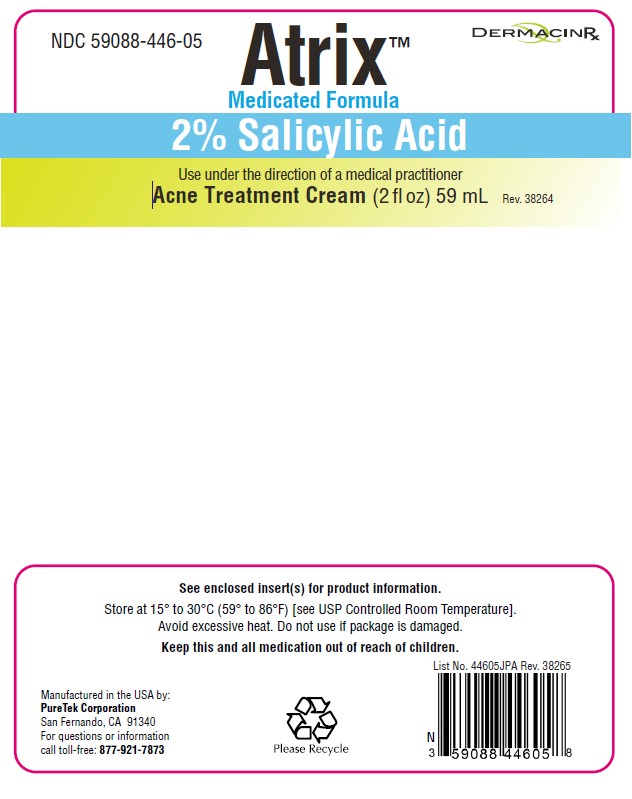 DRUG LABEL: Atrix Acne Treatment
NDC: 59088-446 | Form: CREAM
Manufacturer: PureTek Corporation
Category: otc | Type: HUMAN OTC DRUG LABEL
Date: 20241001

ACTIVE INGREDIENTS: SALICYLIC ACID 20 mg/1 mL
INACTIVE INGREDIENTS: HEXYLENE GLYCOL; OLIGOPEPTIDE-10; PHENOXYETHANOL; BUTYLENE GLYCOL; GLUCOSAMINE HYDROCHLORIDE; CARBOMER HOMOPOLYMER, UNSPECIFIED TYPE; DIMETHICONE; GLYCERIN; GLYCERYL STEARATE SE; LAMINARIA DIGITATA; DIMETHICONE/VINYL DIMETHICONE CROSSPOLYMER (SOFT PARTICLE); .ALPHA.-TOCOPHEROL ACETATE, DL-; CETEARYL OLIVATE; DECYL GLUCOSIDE; SACCHAROMYCES CEREVISIAE; SODIUM HYDROXIDE; SORBITAN OLIVATE; PALMITIC ACID; WATER; UREA; CYCLOMETHICONE 5; ALLYL METHACRYLATE/GLYCOL DIMETHACRYLATE CROSSPOLYMER; CAPRYLYL GLYCOL; STEARIC ACID; .ALPHA.-GLUCAN OLIGOSACCHARIDE; SODIUM ASCORBYL PHOSPHATE; GLYCYRRHIZINATE DIPOTASSIUM; EDETATE DISODIUM; ETHYLHEXYLGLYCERIN

Atrix™ Acne Treatment Cream

Active ingredient

Salicylic Acid 2%

Purpose

Acne Treatment

Uses:

■ for the treatment of acne
■ dries and clears acne pimples, acne blemishes, whiteheads and blackheads
■ helps prevent the development of new acne pimples, acne blemishes, whiteheads and blackheads

Warnings

For external use only

When using this product

■ skin irritation and dryness is more likely to occur if you use another topical acne medication at the same time. If irritation occurs, only use one topical acne medication at a time.

■ rinse right away with water if it gets in eyes.

Stop use and ask a doctor

■ if skin irritation occurs or gets worse

Keep out of reach of children.

If swallowed, get medical help or contact a Poison Control Center right away.

Directions

■ Clean the skin thoroughly before applying this product

■ cover the entire affected area with a thin layer one to three times daily

■ because excessive drying of the skin may occur, start with one application daily, then gradually increase to two or three times daily if needed or as directed by a doctor

■ if bothersome dryness or peeling occurs, reduce application to once a day or every other day.

Use under the direction of a medical practitioner.

Other information

■ protect from freezing

■ avoid excessive heat

Store at 15° to 30°C (59° to 86°F) [see USP Controlled Room Temperature].
Avoid excessive heat. Do not use if package is damaged.
Keep this and all medication out of reach of children.

Inactive ingredients

Allyl Methacrylates Crosspolymer, Aqua (Purified Water), Butylene Glycol, Caprylyl Glycol, Carbomer, Cetearyl Olivate, Cyclopentasiloxane, Decyl Glucoside, Dimethicone, Dipotassium Glycyrrhizinate, Disodium EDTA, Ethylhexylglycerin, Alpha-Glucan Oligosaccharide, Glucosamine HCl, Glycerin, Glyceryl Stearate SE, Hexylene Glycol, Laminaria Digitata (Algae) Extract, Oligopeptide- 10, Palmitic Acid, Phenoxyethanol, Polysilicone-11, Saccharomyces Cerevisiae Extract, Sodium Ascorbyl Phosphate, Sodium Hydroxide, Sorbitan Olivate, Stearic Acid, DL- alpha- Tocopheryl Acetate, Urea

QUESTIONS

Call toll-free:

1-877-921-7873

Atrix Acne Cream

Packaged for :
PureTek Corporation
Panorama City, CA 91402
For questions or information
call toll-free: 877-921-7873